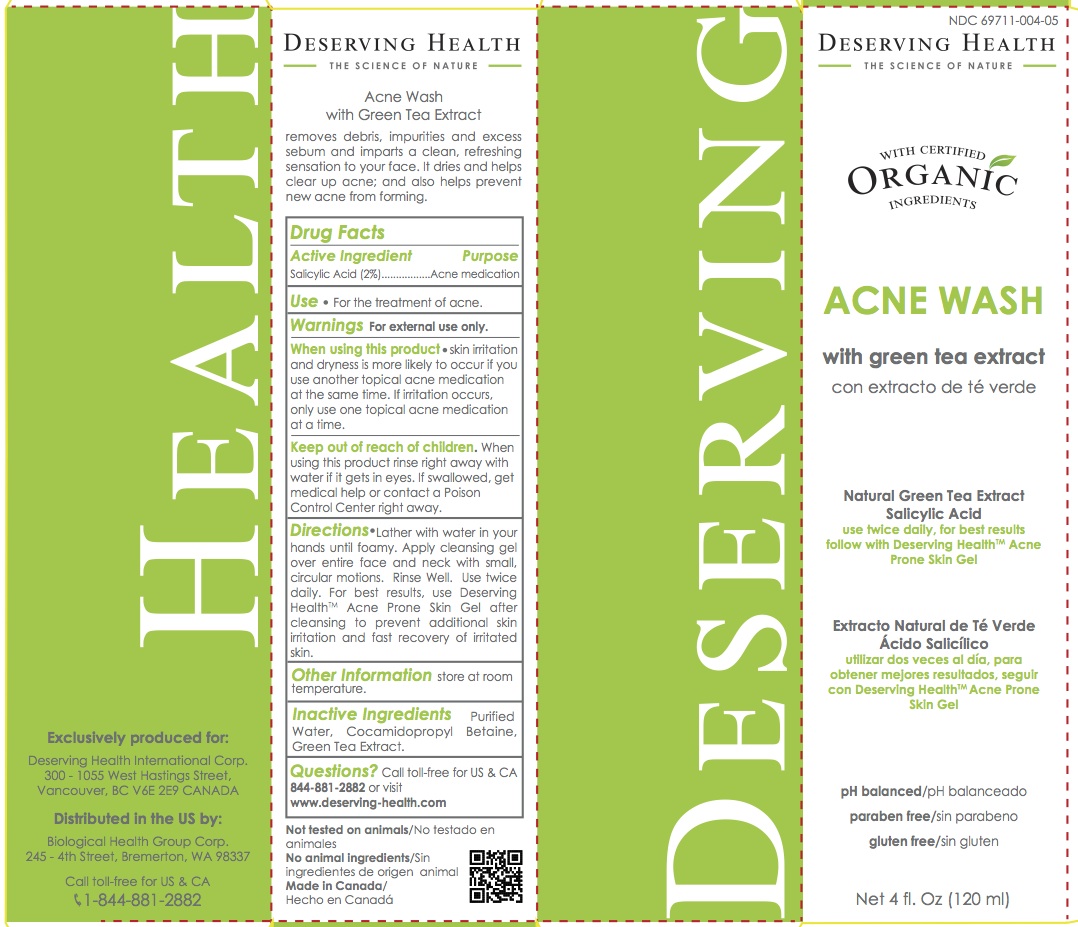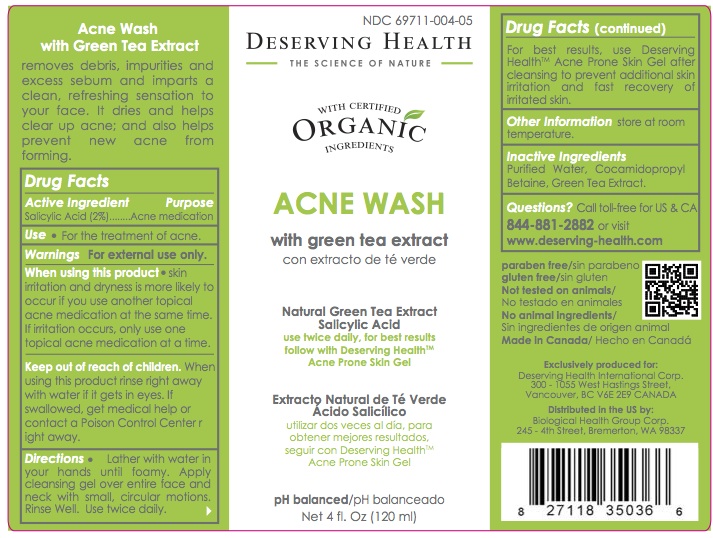 DRUG LABEL: ACNE PRONE
NDC: 69711-004 | Form: GEL
Manufacturer: Biological Health Group Corporation
Category: otc | Type: HUMAN OTC DRUG LABEL
Date: 20150622

ACTIVE INGREDIENTS: SALICYLIC ACID 2 g/100 mL
INACTIVE INGREDIENTS: WATER; COCAMIDOPROPYL BETAINE; GREEN TEA LEAF

ACNE WASH

Active ingredient Purpose

Salicylic Acid – 2% Acne Medication

Purpose

Acne medication

Use

For the treatment of acne

Warnings

For external use only.

When using this product • skin irritation and dryness is more likely to occur if you use another topical acne medication at the same time. If irritation occurs, only use one topical acne medication at a time.

Keep out of reach of the children

When using this product rinse right away with water if it gets in eyes. If swallowed, get medical help or contact a Poison Control Center right away.

Directions

Lather with water in your hands until foamy. Apply cleansing gel over entire face and neck with small, circular motions. Rinse Well. Use twice daily. For best results, use Deserving HealthTM Acne Prone Skin Gel after cleansing to prevent additional skin irritation and fast recovery of irritated skin.

Inactive ingredients

Purified Water, Cocamidopropyl Betaine, Green Tea Extract.

Questions?

Call toll-free from US & CA +1-844-881-2882 or visit www.deserving-health.com

Other Information

Store at room temperature.